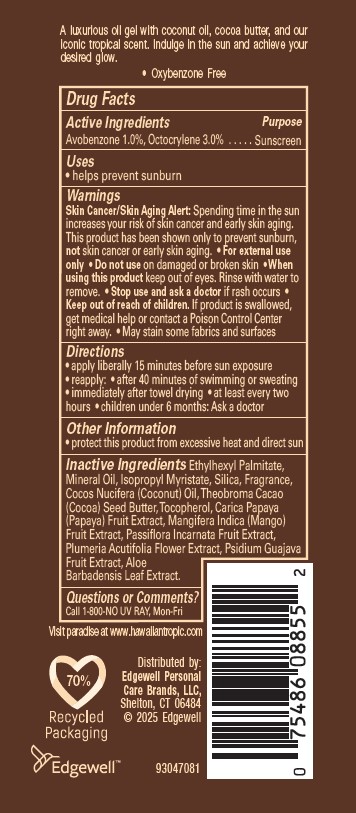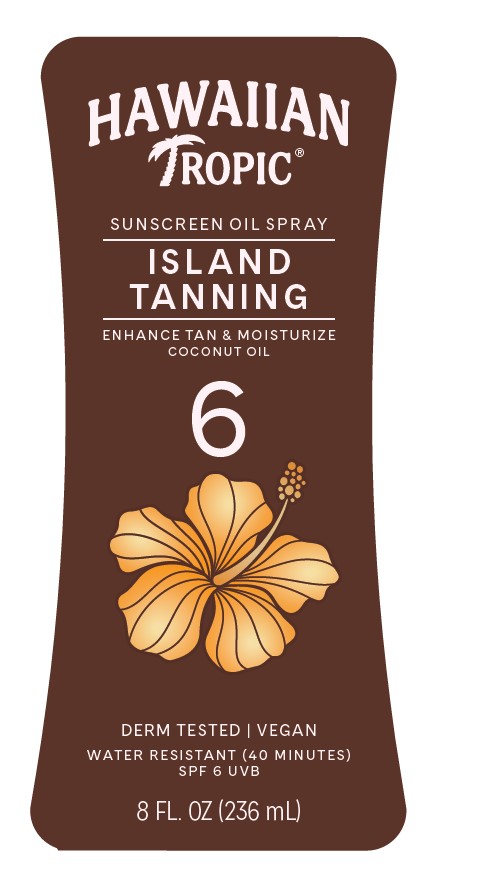 DRUG LABEL: HAWAIIAN TROPIC
NDC: 63354-593 | Form: SPRAY
Manufacturer: Edgewell Personal Care Brands LLC
Category: otc | Type: HUMAN OTC DRUG LABEL
Date: 20250928

ACTIVE INGREDIENTS: OCTOCRYLENE 3 g/100 g; AVOBENZONE 1 g/100 g
INACTIVE INGREDIENTS: COCOA BUTTER; GLYCERYL OLEATE; GUAVA; PASSIFLORA INCARNATA FRUIT; ETHYLHEXYL PALMITATE; ALOE VERA LEAF; MINERAL OIL; ISOPROPYL MYRISTATE; SILICON DIOXIDE; PAPAYA; PLUMERIA RUBRA FLOWER; TOCOPHEROL; MANGO; COCONUT OIL

Active Ingredients

Avobenzone 1.0%, Octocrylene 3.0%

Purpose

Sunscreen

Uses

• helps prevent sunburn

Warnings

Skin Cancer/Skin Aging Alert: Spending time in the sun increases your risk of skin cancer and early skin aging. This product has been shown only to prevent sunburn, not skin cancer or early skin aging.

• For external use only

• May stain some fabrics and surfaces

Do not use

on damaged or broken skin

When using this product

keep out of eyes. Rinse with water to remove.

Stop use and ask a doctor

if rash occurs

Keep out of reach of children.

If product is swallowed, get medical help or contact a Poison Control Center right away.

Directions

• apply liberally 15 minutes before sun exposure • reapply: • after 40 minutes of swimming or sweating • immediately after towel drying • at least every two hours • children under 6 months: Ask a doctor

Other Information

• protect this product from excessive heat and direct sun

Inactive Ingredients

Ethylhexyl Palmitate, Mineral Oil, Isopropyl Myristate, Silica, Fragrance, Cocos Nucifera (Coconut) Oil, Theobroma Cacao (Cocoa) Seed Butter, Tocopherol, Carica Papaya (Papaya) Fruit Extract, Mangifera Indica (Mango) Fruit Extract, Passiflora Incarnata Fruit Extract, Plumeria Acutifolia Flower Extract, Psidium Guajava Fruit Extract, Aloe Barbadensis Leaf Extract.

Questions or Comments?

Call 1-800-NO UV RAY, Mon-Fri

Principal Display Panel

HAWAIIAN
TROPIC(R)
SUNSCREEN OIL SPRAY
ISLAND
TANNING
ENHANCE TAN & MOISTURIZE
COCONUT OIL
6
DERM TESTED | VEGAN
WATER RESISTANT (40 MINUTES)
SPF 6 UVB
8 FL. OZ (236 mL)